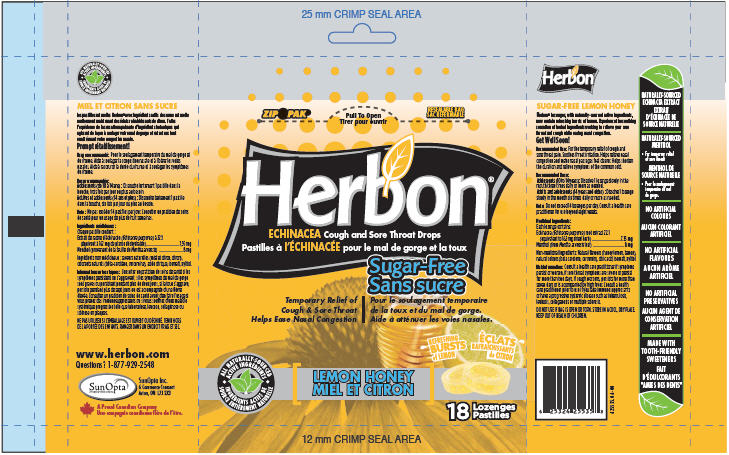 DRUG LABEL: Herbon Sugar Free Lemon Honey
NDC: 44597-5535 | Form: LOZENGE
Manufacturer: Purity Life Division of SunOpta Co.
Category: otc | Type: HUMAN OTC DRUG LABEL
Date: 20091015

ACTIVE INGREDIENTS: Menthol 8 mg/1 1; Echinacea Purpurea 7.35 mg/1 1
INACTIVE INGREDIENTS: Citric Acid Monohydrate 16.93 mg/1 1; Xylitol

INDICATIONS AND USAGE

Recommended Use: For the temporary relief of cough and sore throat pain. Soothes throat irritation. Helps relieve nasal congestion and make nasal passages feel clearer. Helps shorten the duration and relieve symptoms of the common cold.

Recommended Dose:

Adolescents (10 to 14 years): Dissolve 1 lozenge slowly in the mouth three times daily or more as needed.

Adults and adolescents (14 years and older): Dissolve 1 lozenge slowly in the mouth six times daily or more as needed.

Note: Do not exceed 14 lozenges per day. Consult a health care practitioner for use beyond eight weeks.

Medicinal Ingredients:

Each lozenge contains:

Echinacea (Echinacea purpurea) root extract 22:1
(equivalent to 162 mg dried herb) ................................7.35 mg

Menthol (from Mentha arvensis leaf) .................................8 mg

INACTIVE INGREDIENT

Non-medicinal Ingredients: Natural flavours (honey lemon, lemon), natural colours (beta carotene, curcumin), citric acid, isomalt, xylitol.

WARNINGS

Risk Information: Consult a health care practitioner if symptoms persist or worsen, if sore throat symptoms are severe or persist for more than two days, if cough worsens, persists for more than seven days or is accompanied by high fever. Consult a health care practitioner prior to use if you take immunosuppressants or have a progressive systemic disease such as tuberculosis, leukosis, collagenosis or multiple sclerosis.

DO NOT USE IF BAG IS OPEN OR TORN.

STORAGE AND HANDLING

STORE IN A COOL, DRY PLACE.

KEEP OUT OF REACH OF CHILDREN.

PRINCIPAL DISPLAY PANEL - 18 Lozenge Bag

Herbon®

ECHINACEA Cough and Sore Throat Drops

Sugar-Free

Temporary Relief of
Cough & Sore Throat
Helps Ease Nasal Congestion

ALL NATURALLY-SOURCED
ACTIVE INGREDIENTS

LEMON HONEY

REFRESHING
BURSTS
of LEMON

18 Lozenges